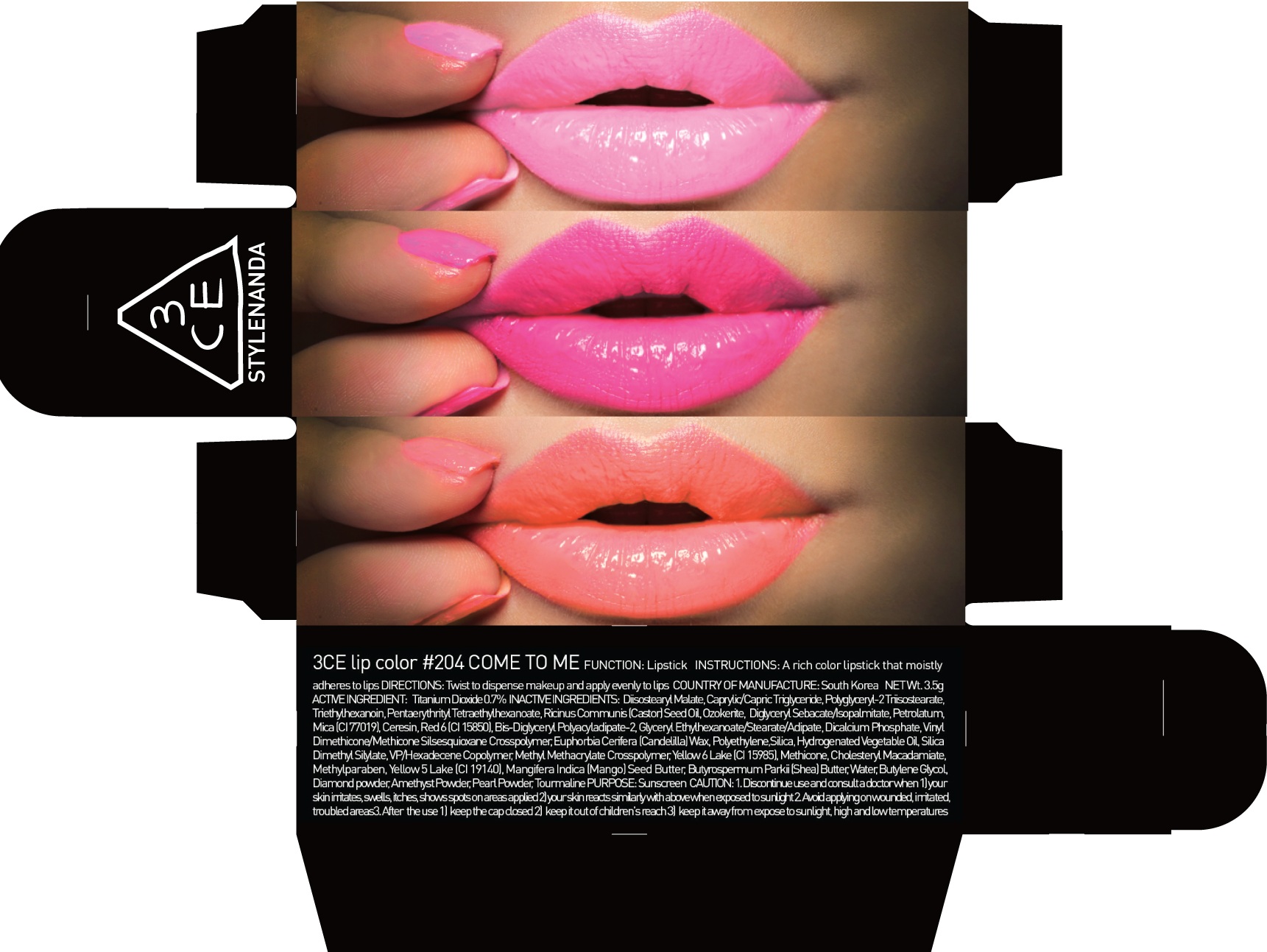 DRUG LABEL: 3CE LIP COLOR 204 COME TO ME
NDC: 60764-067 | Form: LIPSTICK
Manufacturer: Nanda Co., Ltd
Category: otc | Type: HUMAN OTC DRUG LABEL
Date: 20161005

ACTIVE INGREDIENTS: Titanium Dioxide 0.02 g/3.5 g
INACTIVE INGREDIENTS: Diisostearyl Malate; Triethylhexanoin

ACTIVE INGREDIENT

Active Ingredient: Titanium Dioxide 0.7%

INACTIVE INGREDIENT

Inactive Ingredients: Diisostearyl Malate, Caprylic/Capric Triglyceride, Polyglyceryl-2 Triisostearate, Triethylhexanoin, Pentaerythrityl Tetraethylhexanoate, Ricinus Communis (Castor) Seed Oil, Ozokerite, Diglyceryl Sebacate/Isopalmitate, Petrolatum, Mica (CI 77019), Ceresin, Red 6 (CI 15850), Bis-Diglyceryl Polyacyladipate-2, Glyceryl Ethylhexanoate/Stearate/Adipate, Dicalcium Phosphate, Vinyl Dimethicone/Methicone Silsesquioxane Crosspolymer, Euphorbia Cerifera (Candelilla) Wax, Polyethylene, Silica, Hydrogenated Vegetable Oil, Silica Dimethyl Silylate, VP/Hexadecene Copolymer, Methyl Methacrylate Crosspolymer, Yellow 6 Lake (CI 15985), Methicone, Cholesteryl Macadamiate, Methylparaben, Yellow 5 Lake (CI 19140), Mangifera Indica (Mango) Seed Butter, Butyrospermum Parkii (Shea) Butter, Water, Butylene Glycol, Diamond powder, Amethyst Powder, Pearl Powder, Tourmaline

PURPOSE

Purpose: Sunscreen

CAUTION

CAUTION: 1. Discontinue use and consult a doctor when - your skin irritates, swells, itches, shows spots on areas applied - your skin reacts similarly with above when exposed to sunlight 2. Avoid applying on wounded, irritated, troubled areas 3. After the use - keep the cap closed - keep it out of children's reach - keep it away from expose to sunlight, high and low temperatures

DESCRIPTION

INSTRUCTIONS: A rich color lipstick that moistly adheres to lips.

Directions: Twist to dispense makeup and apply evenly to lips